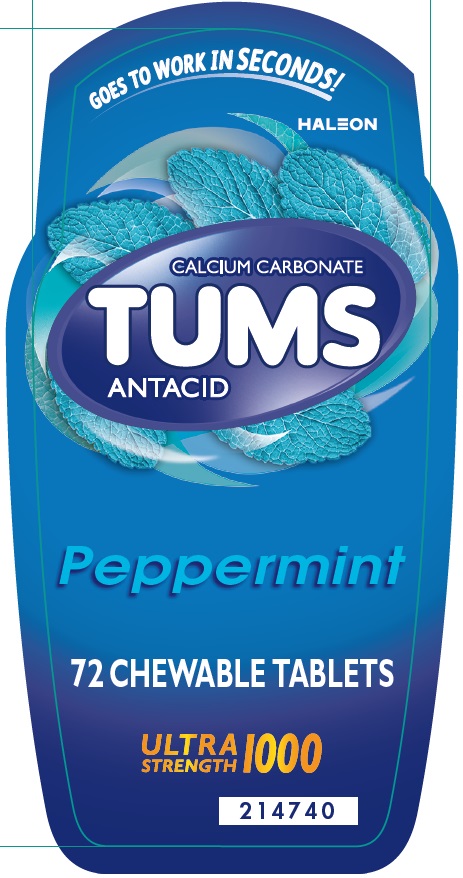 DRUG LABEL: TUMS
NDC: 0135-0235 | Form: TABLET, CHEWABLE
Manufacturer: Haleon US Holdings LLC
Category: otc | Type: HUMAN OTC DRUG LABEL
Date: 20250226

ACTIVE INGREDIENTS: CALCIUM CARBONATE 1000 mg/1 1
INACTIVE INGREDIENTS: ACACIA; STARCH, CORN; CROSPOVIDONE, UNSPECIFIED; DEXTRIN, CORN; DEXTROSE, UNSPECIFIED FORM; MAGNESIUM STEARATE; MALTODEXTRIN; MODIFIED CORN STARCH (1-OCTENYL SUCCINIC ANHYDRIDE); SUCROSE; TALC; TRICALCIUM PHOSPHATE

Drug Facts

Active ingredient (in each tablet)

Calcium carbonate 1000 mg

Purpose

Antacid

Uses

relieves

- heartburn
- acid indigestion
- sour stomach
- upset stomach associated with these symptoms

Warnings

Ask a doctor or pharmacist before use if you are

presently taking a prescription drug. Antacids may interact with certain prescription drugs.

When using this product

- do not take more than 7 tablets in 24 hours
- if pregnant do not take more than 5 tablets in 24 hours
- do not use the maximum dosage for more than 2 weeks except under the advice and supervision of a doctor

Directions

- adults and children 12 years of age and over: chew 2-3 tablets as symptoms occur, or as directed by a doctor. Chew or crush tablets completely before swallowing.
- do not take for symptoms that persist for more than 2 weeks unless advised by a doctor

Other information

- each tablet contains: elemental calcium 390 mg, magnesium 10 mg
- store below 30oC (86oF)

Inactive ingredients

acacia, corn starch, crospovidone, dextrin, dextrose, flavors, magnesium stearate, maltodextrin, modified corn starch, sucrose, talc, tricalcium phosphate

Questions?

1-800-897-7535

Generic Section

Do not use if printed inner safety seal under cap is broken or missing.

Principal Display Panel

GOES TO WORK IN SECONDS!

CALCIUM CARBONATE

TUMS

ANTACID

Peppermint

72 CHEWABLE TABLETS

ULTRA STRENGTH 1000